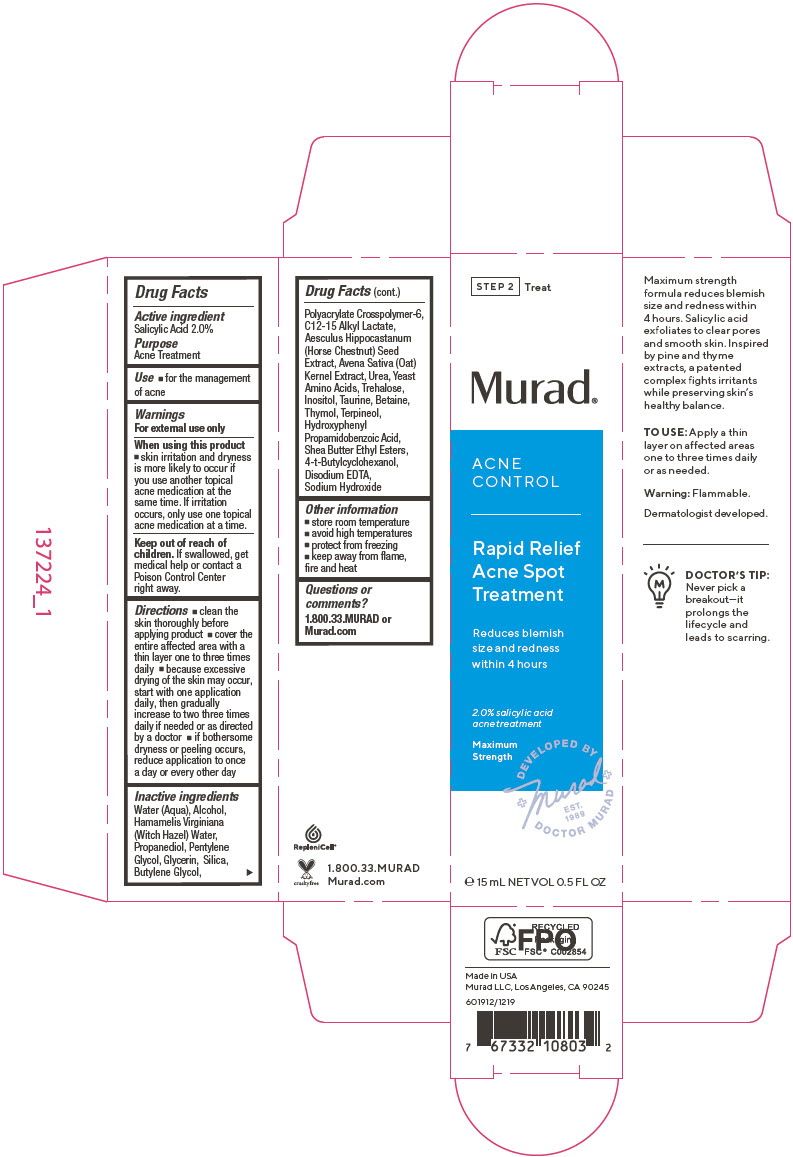 DRUG LABEL: Acne Control Rapid Relief Acne Spot Treatment
NDC: 70381-117 | Form: SOLUTION
Manufacturer: Murad, LLC
Category: otc | Type: HUMAN OTC DRUG LABEL
Date: 20210706

ACTIVE INGREDIENTS: SALICYLIC ACID 2 g/100 mL
INACTIVE INGREDIENTS: WATER; ALCOHOL; HAMAMELIS VIRGINIANA TOP WATER; PROPANEDIOL; PENTYLENE GLYCOL; GLYCERIN; SILICON DIOXIDE; BUTYLENE GLYCOL; AMMONIUM ACRYLOYLDIMETHYLTAURATE, DIMETHYLACRYLAMIDE, LAURYL METHACRYLATE AND LAURETH-4 METHACRYLATE COPOLYMER, TRIMETHYLOLPROPANE TRIACRYLATE CROSSLINKED (45000 MPA.S); C12-15 ALKYL LACTATE; HORSE CHESTNUT; OAT; UREA; AMINO ACIDS, SOURCE UNSPECIFIED; TREHALOSE; INOSITOL; TAURINE; BETAINE; THYMOL; TERPINEOL; HYDROXYPHENYL PROPAMIDOBENZOIC ACID; SHEA BUTTER ETHYL ESTERS; 4-TERT-BUTYLCYCLOHEXANOL; EDETATE DISODIUM ANHYDROUS; SODIUM HYDROXIDE

Acne Control Rapid Relief Acne Spot Treatment

Drug Facts

Active ingredient

Salicylic Acid 2.0%

Purpose

Acne Treatment

Use

- for the management of acne

Warnings

For external use only

When using this product

- skin irritation and dryness is more likely to occur if you use another topical acne medication at the same time. If irritation occurs, only use one topical acne medication at a time.

Keep out of reach of children. If swallowed, get medical help or contact a Poison Control Center right away.

Directions

- clean the skin thoroughly before applying product
- cover the entire affected area with a thin layer one to three times daily
- because excessive drying of the skin may occur, start with one application daily, then gradually increase to two three times daily if needed or as directed by a doctor
- if bothersome dryness or peeling occurs, reduce application to once a day or every other day

Inactive ingredients

Water (Aqua), Alcohol, Hamamelis Virginiana (Witch Hazel) Water, Propanediol, Pentylene Glycol, Glycerin, Silica, Butylene Glycol, Polyacrylate Crosspolymer-6, C12-15 Alkyl Lactate, Aesculus Hippocastanum (Horse Chestnut) Seed Extract, Avena Sativa (Oat) Kernel Extract, Urea, Yeast Amino Acids, Trehalose, Inositol, Taurine, Betaine, Thymol, Terpineol, Hydroxyphenyl Propamidobenzoic Acid, Shea Butter Ethyl Esters, 4-t-Butylcyclohexanol, Disodium EDTA, Sodium Hydroxide

Other information

- store room temperature
- avoid high temperatures
- protect from freezing
- keep away from flame, fire and heat

Questions or comments?

1.800.33.MURAD or Murad.com

PRINCIPAL DISPLAY PANEL - 15 mL Tube Carton

STEP 2
Treat

Murad®

ACNE
CONTROL

Rapid Relief
Acne Spot
Treatment

Reduces blemish
size and redness
within 4 hours

2.0% salicylic acid
acne treatment

Maximum
Strength

DEVELOPED BY
+Murad+
EST.
1989
DOCTOR MURAD

℮ 15 mL NET VOL 0.5 FL OZ